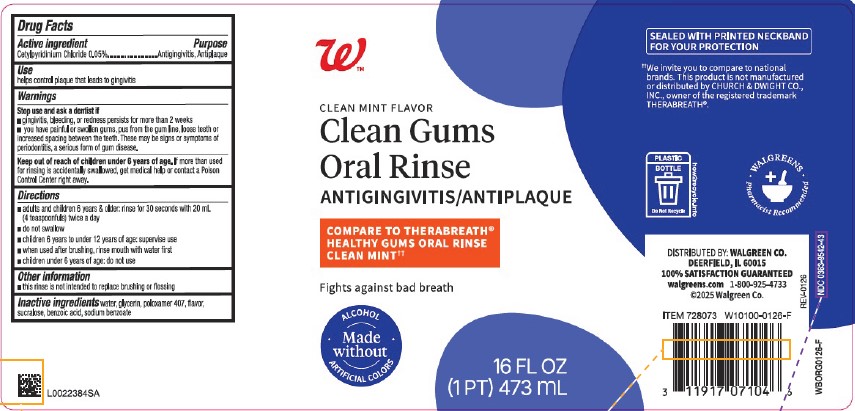 DRUG LABEL: Cetylpyridinium Chloride
NDC: 0363-9542 | Form: LIQUID
Manufacturer: Walgreen Co.
Category: otc | Type: HUMAN OTC DRUG LABEL
Date: 20260211

ACTIVE INGREDIENTS: CETYLPYRIDINIUM CHLORIDE 0.5 mg/1 mL
INACTIVE INGREDIENTS: WATER; GLYCERIN; POLOXAMER 407; SUCRALOSE; BENZOIC ACID; SODIUM BENZOATE

Walgreens 542.000/542AA
Clean Gums Oral Rinse

Active ingredient

Cetylpyridinium Chloride 0.05%

Purpose

Antigingivitis, Antiplaque

Use

helps control plaque that leads to gingivitis

Warnings

for this product

Stop use and ask a dentist if

- gingivitis, bleeding, or redness persists for more than 2 weeks
- you have painful or swollen gums, pus from the gum line, loose teeth or increased spacing between the teeth. These may be signs or symptoms of periodontitis, a serious form of gum disease.

Keep out of reach of children under 6 years of age.

If more than used for rinsing is accidentally swallowed, get medical help or contact a Poison Control Center right away.

Directions

- adults and children 6 years & older: rinse for 30 seconds with 20 mL (4 teaspoonfuls) twice a day
- do not swallow
- children 6 years to under 12 years of age: supervise use
- when used after brushing, rinse mouth with water first
- children under 6 years of age: do not use

Other information

- this rinse is not intended to replace brushing or flossing

Inactive ingredients

water, glycerin, poloxamer 407, flavor, sucralose, benzoic acid, sodium benzoate

Tamper Evident Statement

Sealed with printed neckband for your protection

Disclaimer

‡We invite you to compare to national brands. This product is not manufactured or distributed by Church & Dwight Co., Inc. owner of the registered trademark TheraBreath®.

Adverse Reaction

PLASTIC BOTTLE

Do Not Recycle

how2recycle.info

WALGREENS Pharmacist Recommended

DISTRIBUTED BY: WALGREEN CO.

DEERFIELD, IL 60015

100% SATISFACTION GUARANTEED

walgreens.com 1-800-925-4733

©2025 Walgreen Co.

NDC 0363-9542-43

Principal Display Panel

W™

CLEAN MINT FLAVOR

Clean Gums

Oral Rinse

ANTIGINGIVITIS/ANTIPLAQUE

COMPARE TO THERABREATH®HEALTHY GUMS ORAL RINSE CLEAN MINT‡

Fights against bad breath

Made Without

- ALCOHOL
- ARTIFICIAL COLORS

16 FL OZ (1 PT) 473 mL